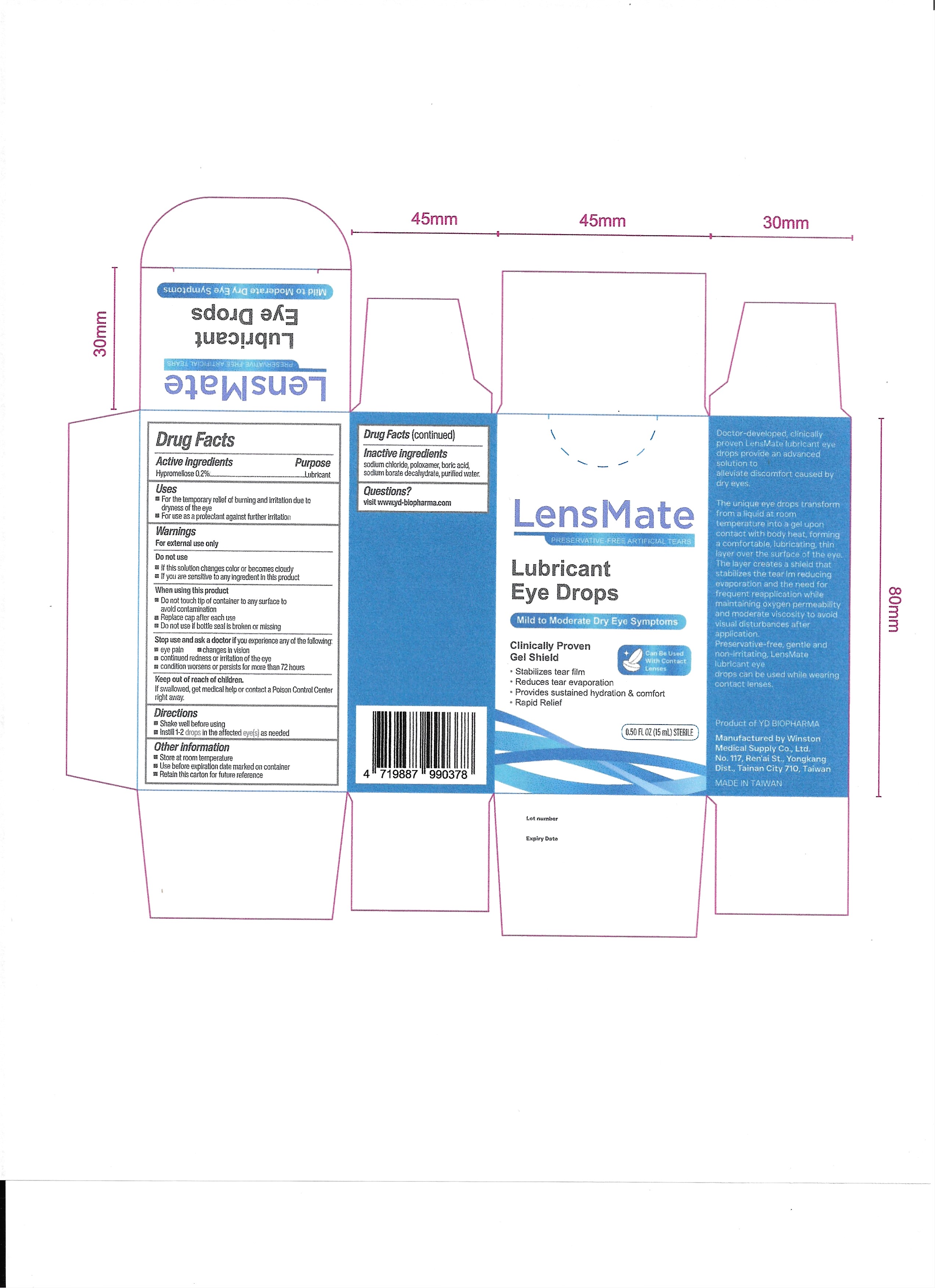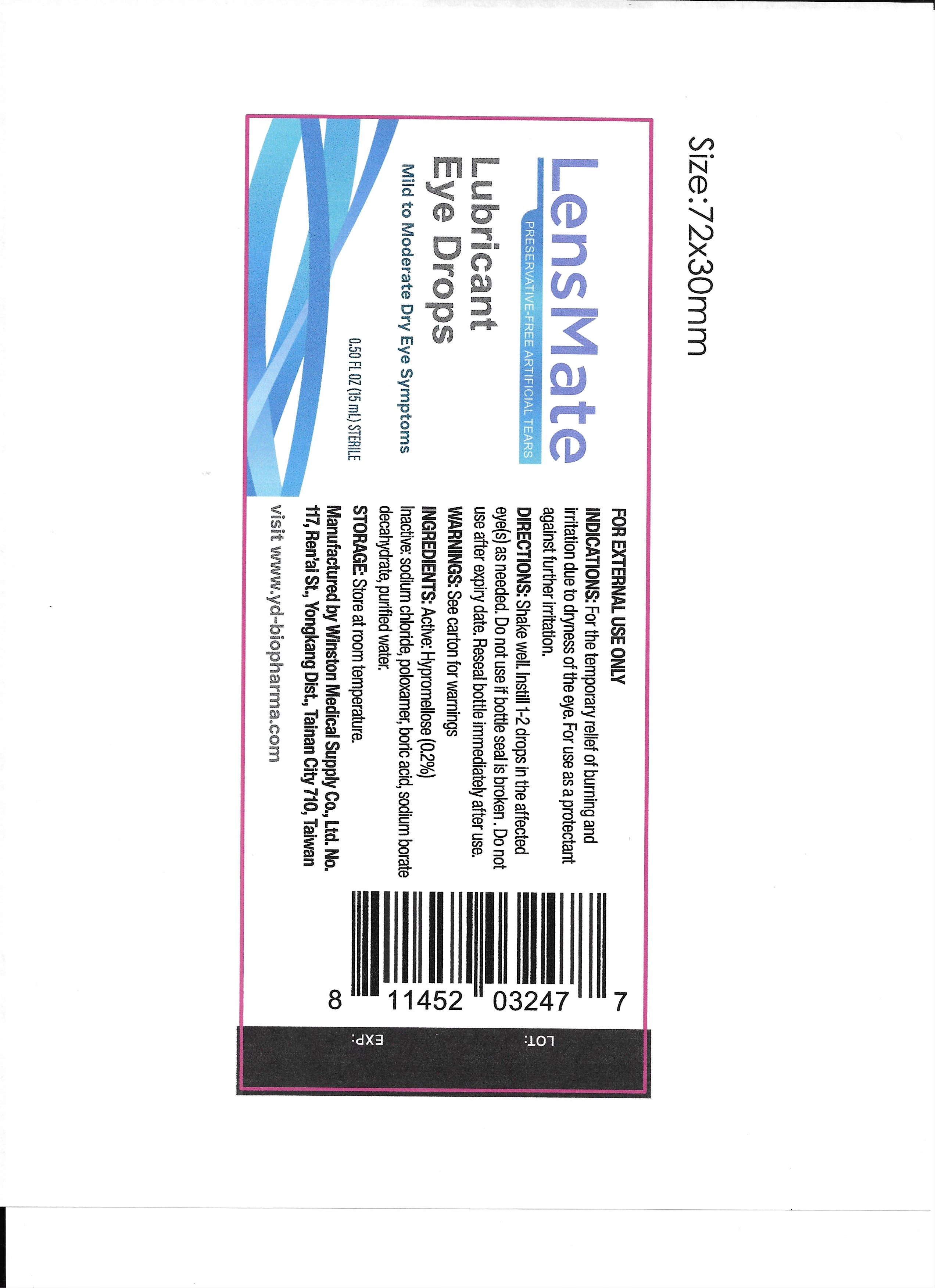 DRUG LABEL: LensMate Preservative-Free Artificial Tears
NDC: 87106-001 | Form: LIQUID
Manufacturer: YD BIO USA, INC.
Category: otc | Type: HUMAN OTC DRUG LABEL
Date: 20250915

ACTIVE INGREDIENTS: HYPROMELLOSES 0.2 g/100 g
INACTIVE INGREDIENTS: POLOXAMER 188; SODIUM CHLORIDE; BORIC ACID; SODIUM BORATE; WATER

001-01

ACTIVE INGREDIENT

Hypromellose 0.2%

PURPOSE

Lubricant

Stop use and ask a doctor if you experience any of the following:

Eye pain
Changes in vision
Continued redness or irritation of the eye
Condition worsens or persists for more than 72 hours

DO NOT USE

If this solution changes color or becomes cloudy
If you are sensitive to any ingredient in this product

KEEP OUT OF REACH OF CHILDREN

If swallowed, get medical help or contact a Poison Control Center right away.

Stop use and ask a doctor if you experience any of the following:

eye pain
Changes in vision
Continued redness or irritation of the eye
Condition worsens or persists for more than 72 hours

WHEN USING

Do not touch tip of container to any surface to avoid contamination
Replace cap after each use
Do not use if bottle seal is broken or missing

OTHER SAFETY INFORMATION

Store at room temperature
Use before expiration date marked on container
Retain this carton for future reference

INACTIVE INGREDIENT

Sodium chloride, poloxamer, boric acid, sodium borate decahydrate, purified water.

QUESTIONS

Visit www.yd-biopharma.com

INSTRUCTIONS FOR USE

Shake well before using
Instill 1-2 drops in the affected eye(s) as needed

Directions

Shake well before using
Instill 1-2 drops in the affected eye(s) as needed

WARNINGS

For external use only

INDICATIONS AND USAGE

For the temporary relief of burning and irritation due to dryness of the eye
For use as a protectant against further irritation